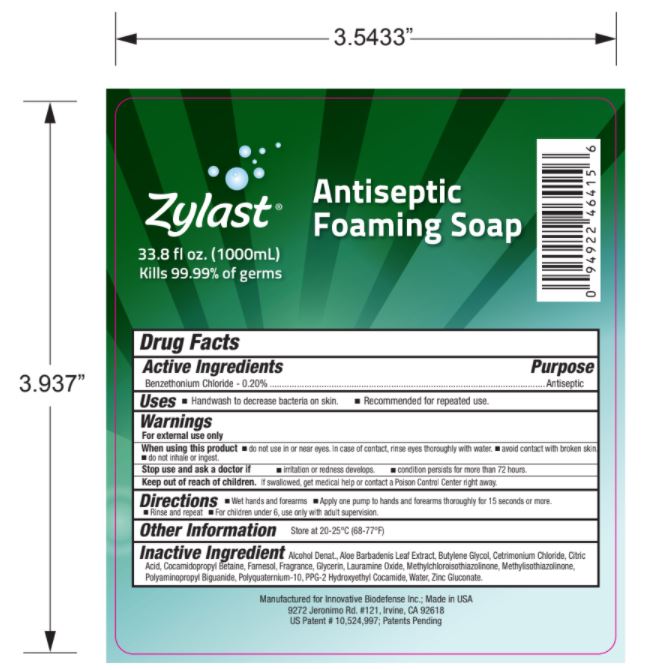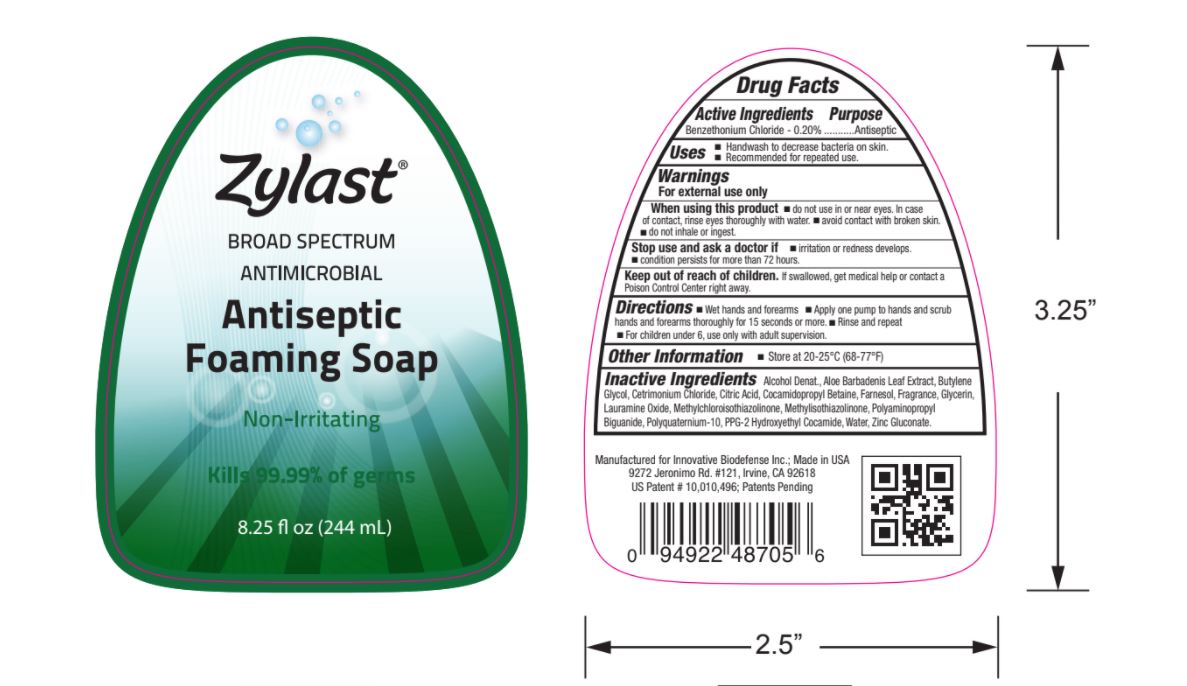 DRUG LABEL: ZylastXP Antiseptic Foaming
NDC: 57362-467 | Form: SOAP
Manufacturer: Innovative Biodefense
Category: otc | Type: HUMAN OTC DRUG LABEL
Date: 20230101

ACTIVE INGREDIENTS: BENZETHONIUM CHLORIDE 2 mg/1 mL
INACTIVE INGREDIENTS: FARNESOL; GLYCERIN; METHYLCHLOROISOTHIAZOLINONE; POLIHEXANIDE; WATER; LAURAMINE OXIDE; COCAMIDOPROPYL BETAINE; CETRIMONIUM CHLORIDE; BUTYLENE GLYCOL; CITRIC ACID MONOHYDRATE; ZINC GLUCONATE; PPG-2 HYDROXYETHYL COCAMIDE

Zylast
Foaming Soap

Active Ingredients

Benzethonium Chloride - 0.20%

Purpose

Antiseptic

Uses

- Handwash to decrease bacteria on the skin.
- Recommended for repeated use.

Warnings

- For external use only.
- When using this product, do not use in or near eyes. In case of contact, rinse eyes throroughly with water. Avoid contact with broken skin. Do not inhale or ingest.

Stop use and ask a doctor if

Irritation or redness develops.

Condition persists for more than 72 hours.

Keep out of reach of children.

If swallowed, get medical help or contact a Poison Control Center right away.

Directions

- Wet hands and forearms. Apply one pump to hands and forearms thoroughly for 15 seconds or more. Rinse and repeat. For children under 6, use only with adult supervision.

Other Inforamtion

- Store at 20-25°C (68-77°F)

Inactive ingredients

Alcohol Denatured, Aloe Barbadenis Lead Extract, Butylene Glycol, Cetrimonium Chloride, Citric Acid, Cocamidopropyl Betaiine, Farnesol, Fragrance, Glycerin, Lauramine Oxide, Methylchloroisothiazolinone, Methylisothiazolinone, Polyaminopropyl Biguanide, Polyquaternium-10, PPG-12 Hydroxyethyl Cocamide, Water, Zinc Gluconate

RECENT MAJOR CHANGES

- Uses section
- Warnings section
- Inactive Ingredients section
- Directions section

Package/Label Principal Display Panel

NDC 57362-467-01
Zylast
Extended Protection
Broad Spectrum
Antimicrobial
Antiseptic
Foaming Soap
8.25 oz

Package/Label Principal Display Panel

NDC 57362-467-02
Zylast
Extended Protection
Broad Spectrum
Antimicrobial
Antiseptic

Foaming Soap
1000mL (33.8oz)